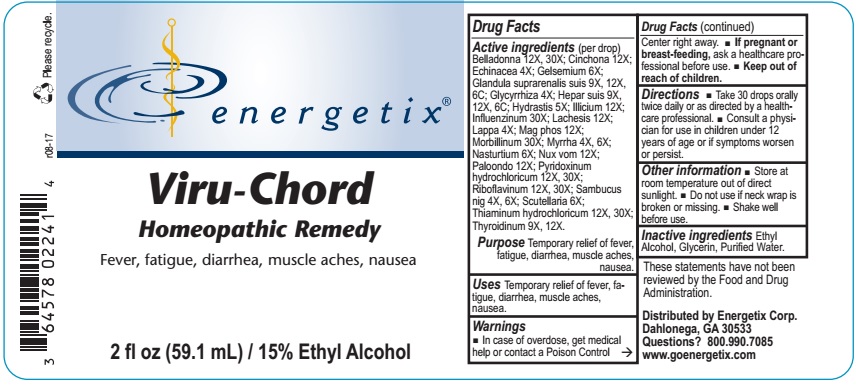 DRUG LABEL: Viru-Chord
NDC: 64578-0078 | Form: LIQUID
Manufacturer: Energetix Corp
Category: homeopathic | Type: HUMAN OTC DRUG LABEL
Date: 20171219

ACTIVE INGREDIENTS: ATROPA BELLADONNA 12 [hp_X]/59.1 mL; CINCHONA OFFICINALIS BARK 12 [hp_X]/59.1 mL; ECHINACEA ANGUSTIFOLIA 4 [hp_X]/59.1 mL; GELSEMIUM SEMPERVIRENS ROOT 6 [hp_X]/59.1 mL; SUS SCROFA ADRENAL GLAND 9 [hp_X]/59.1 mL; GLYCYRRHIZA GLABRA 4 [hp_X]/59.1 mL; PORK LIVER 9 [hp_X]/59.1 mL; GOLDENSEAL 4 [hp_X]/59.1 mL; STAR ANISE 12 [hp_X]/59.1 mL; INFLUENZA A VIRUS 30 [hp_X]/59.1 mL; INFLUENZA B VIRUS 30 [hp_X]/59.1 mL; LACHESIS MUTA VENOM 12 [hp_X]/59.1 mL; ARCTIUM LAPPA ROOT 4 [hp_X]/59.1 mL; MAGNESIUM PHOSPHATE, DIBASIC 12 [hp_X]/59.1 mL; MEASLES VIRUS 30 [hp_X]/59.1 mL; MYRRH 4 [hp_X]/59.1 mL; RORIPPA NASTURTIUM-AQUATICUM 6 [hp_X]/59.1 mL; LARREA TRIDENTATA TOP 12 [hp_X]/59.1 mL; STRYCHNOS NUX-VOMICA SEED 12 [hp_X]/59.1 mL; PYRIDOXINE HYDROCHLORIDE 12 [hp_X]/59.1 mL; RIBOFLAVIN 12 [hp_X]/59.1 mL; SAMBUCUS NIGRA FLOWERING TOP 4 [hp_X]/59.1 mL; SCUTELLARIA LATERIFLORA 6 [hp_X]/59.1 mL; THIAMINE HYDROCHLORIDE 12 [hp_X]/59.1 mL; THYROID, UNSPECIFIED 9 [hp_X]/59.1 mL
INACTIVE INGREDIENTS: WATER 41.359 mL/59.1 mL; ALCOHOL 8.86 mL/59.1 mL; GLYCERIN 8.86 mL/59.1 mL

Viru-Chord

ACTIVE INGREDIENT

Active Ingredients (per drop) Belladonna 12X, 30X; Cinchona 12X; Echinacea 4X; Gelsemium 6X; Glandula suprarenalis suis 9X, 12X, 6C; Glycyrrhiza 4X; Hepar suis 9X, 12X, 6C; Hydrastis 4X; Illicium 12X; Influenzinum 30X; Lachesis 12X; Lappa 4X; Mag phos 12X; Morbillinum 30X; Myrrha 4X, 6X; Nasturtium 6X; Nux vom 12X; Paloondo 12X; Pyridoxinum hydrochloricum 12X, 30X; Riboflavinum 12X, 30X; Sambucus nig 4X, 6X; Scutellaria 6X; Thiaminum hydrochloricum 12X, 30X; Thyroidinum 9X, 12X, 6C

INDICATIONS AND USAGE

Uses Temporary relief of fever, fatigue, diarrhea, muscle aches, nausea.

These statements have not been reviewed by the Food and Drug Administration.

Warnings

- In case of overdose, get medical help or contact a Poison Control Center right away.
- If pregnant or breast feeding, ask a health professional before use.

- KEEP OUT OF REACH OF CHILDREN.

Directions

- Take 30 drops orally twice daily or as directed by a healthcare professional.
- Consult a physician for use in children under 12 years of age or if symptoms worsen or persist.

Other Information

- Store at room temperature out of direct sunlight.
- Do not use if neck wrap seal is broken or missing.

- Shake well before use.

Inactive Ingredients Ethyl Alcohol, Glycerin, Purified Water.

QUESTIONS

Distributed by Energetix Corp.

Dahlonega, GA 30533

Questions? 800.990.7085

www.goenergetix.com

PACKAGE LABEL

energetix

VIRU-CHORD

HomeopathicRemedy

fever, fatigue, diarrhea, muscle aches, nausea.

2 fl oz (59.1 mL) / 15% Ethyl Alcohol

PURPOSE

Relief of fever, fatigue, diarrhea, muscle aches, nausea.